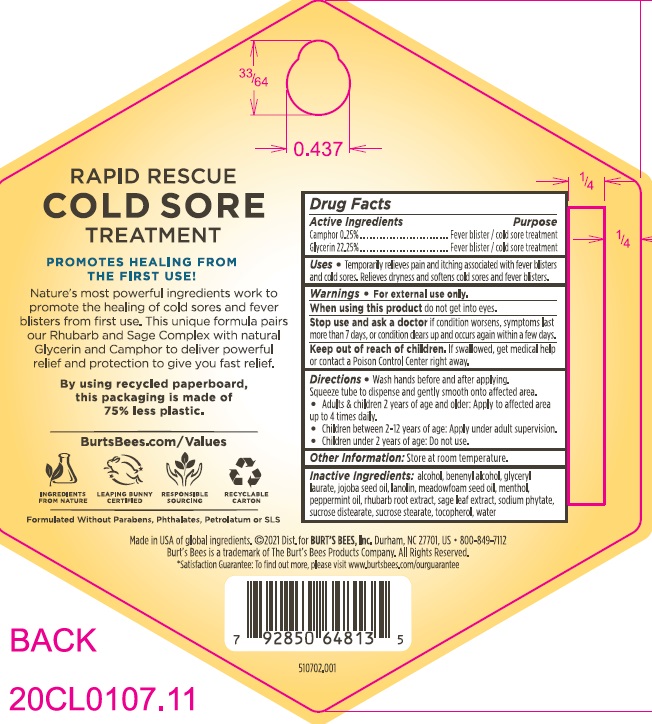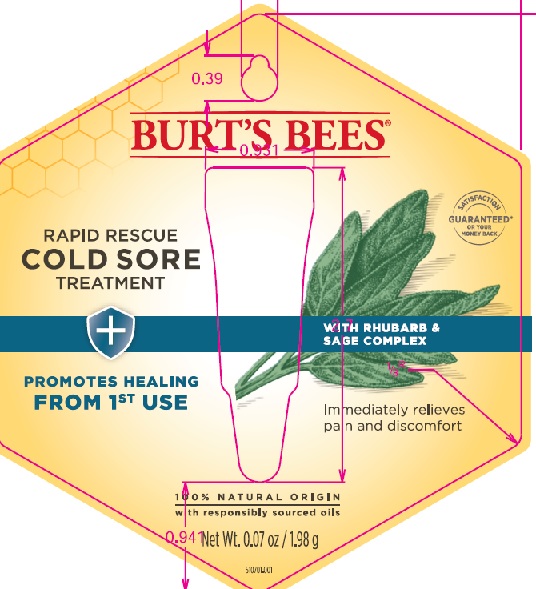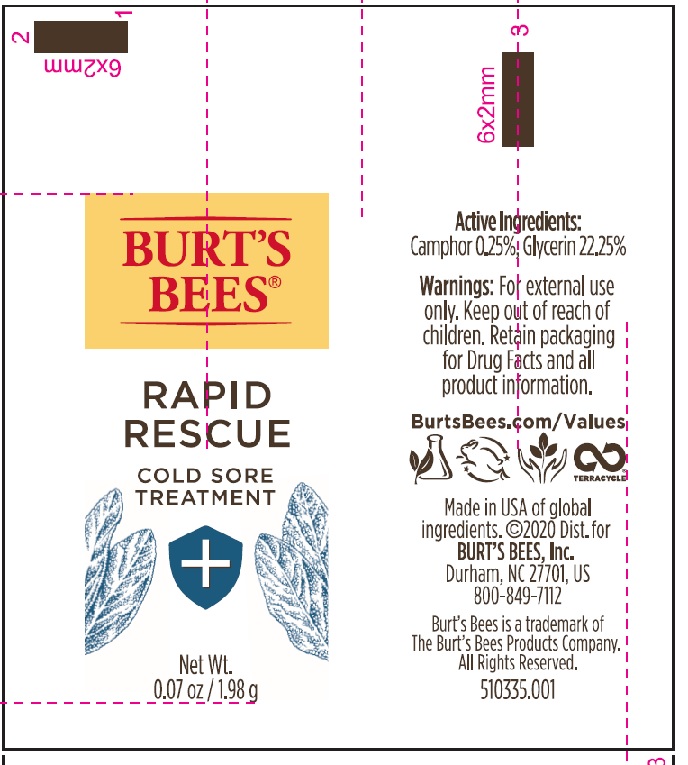 DRUG LABEL: Burts Bees Rapid Rescue Cold Sore Treatment
NDC: 26052-489 | Form: OINTMENT
Manufacturer: Burts Bees
Category: otc | Type: HUMAN OTC DRUG LABEL
Date: 20241203

ACTIVE INGREDIENTS: CAMPHOR (NATURAL) 0.25 g/100 g; GLYCERIN 22.25 g/100 g
INACTIVE INGREDIENTS: DOCOSANOL; WATER; LANOLIN; SUCROSE DISTEARATE; SUCROSE STEARATE; GLYCERYL LAURATE; MENTHA PIPERITA; ALCOHOL; MENTHOL; RHEUM PALMATUM ROOT; SAGE; MEADOWFOAM SEED OIL; JOJOBA OIL; TOCOPHEROL; PHYTATE SODIUM

Burt's Bees Rapid Rescue Cold Sore Treatment

Active Ingredients

Camphor 0.25%......... fever blister/cold sore treatment

Glycerin 22.25%......... fever blister/cold sore treatment

PURPOSE

fever blister/cold sore treatment

Uses

Temporarily relieves pain and itching associated with fever blisters and cold sores. Relieves dryness and softens cold sores and fever blisters

Warnings

For external use only

When using this product

do not get into eyes.

Stop Use and ask a doctor

if condition worses, symptoms last more than 7 days, or condition clears up and occurs again within a few days.

Keep out of reach of children

If swallowed, get medical help or contact a Poison Control Center right away.

Directions

- Wash hands before and after applying

squeeze tube to dispense and gently smooth onto affected area.

- Adults & children 2 years of age and older: Apply to affected area up to 4 times daily.

- Children between 2-12 years of age:Apply under adult supervision

- Children under 2 years of age: Do not use.

Other Information

Store at room temperature

Inactive Ingredients

alcohol, behenyl alcohol, glyceryl laurate, jojoba seed oil, lanolin, meadowfoam seed oil, menthol, pepperming oil, rhubarb root extract, sage leaf extract, sodium phytate, sucrose distearate, sucrose stearate, tocopherol, water